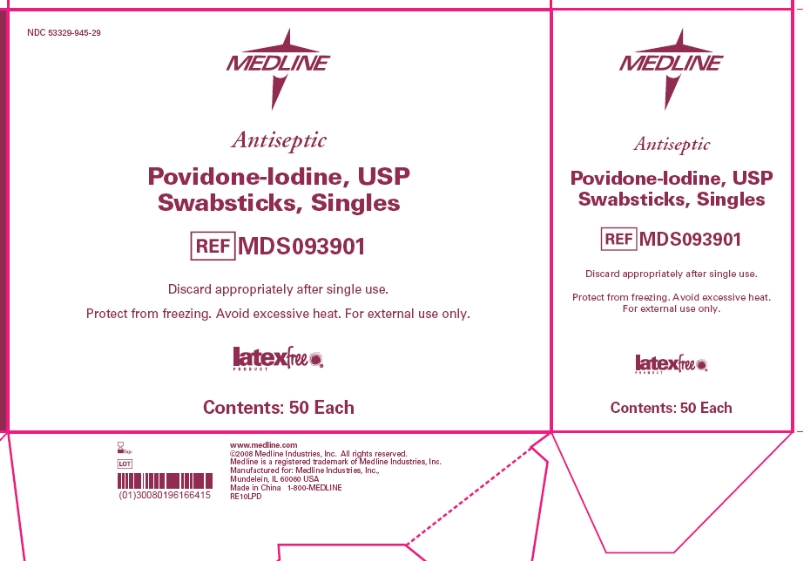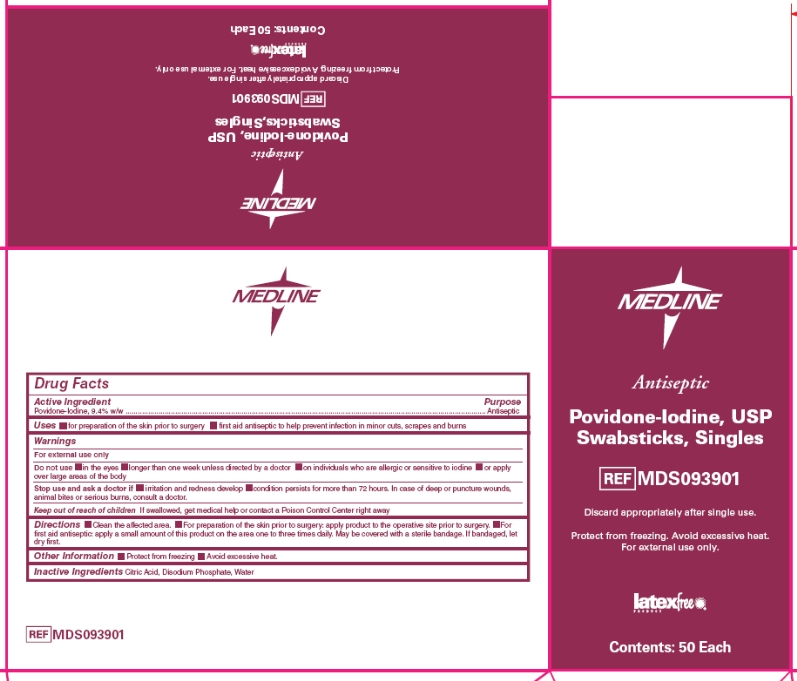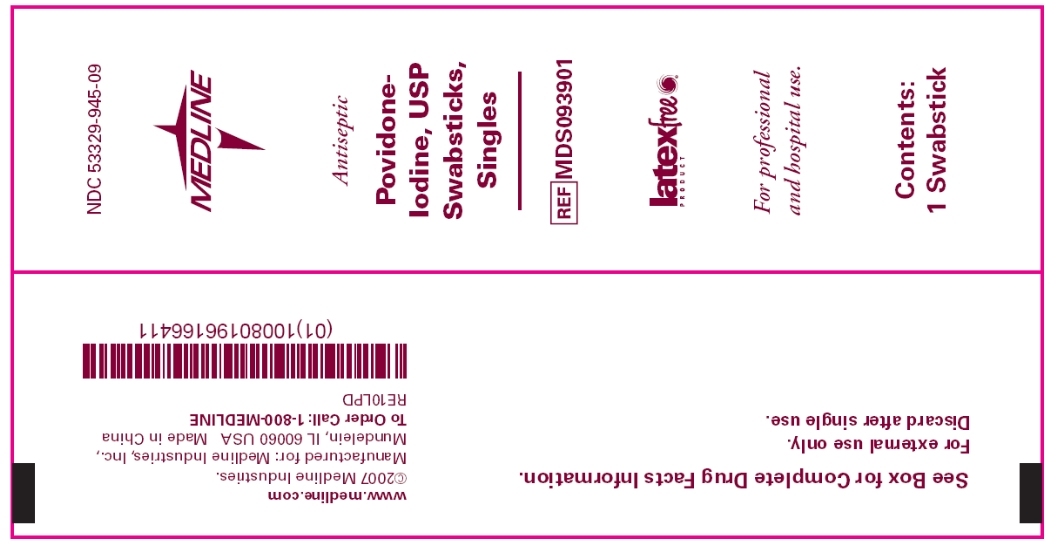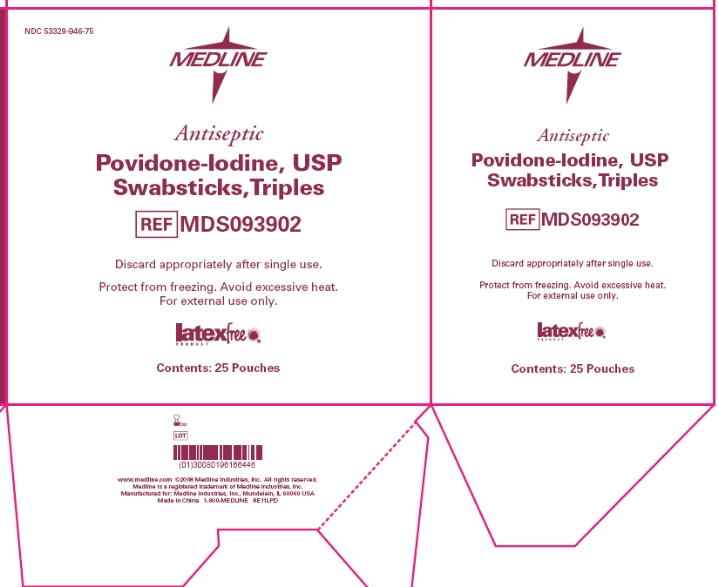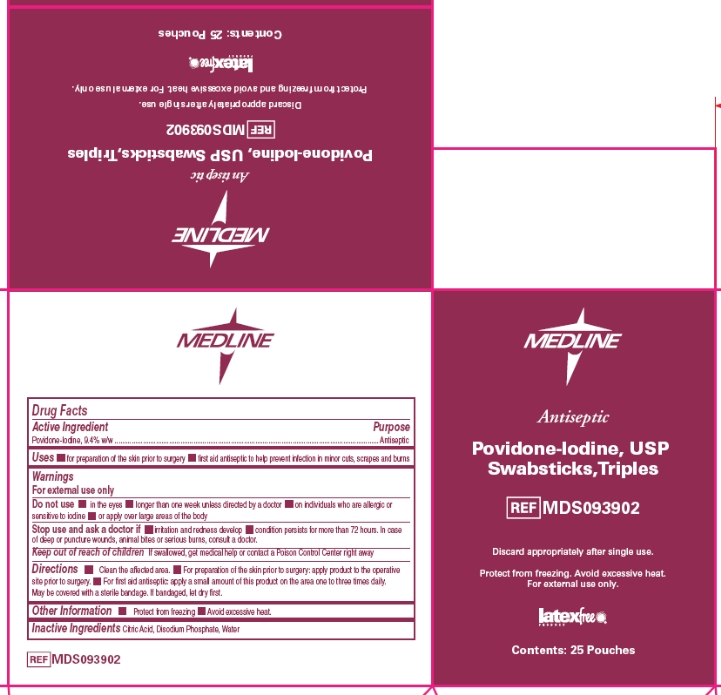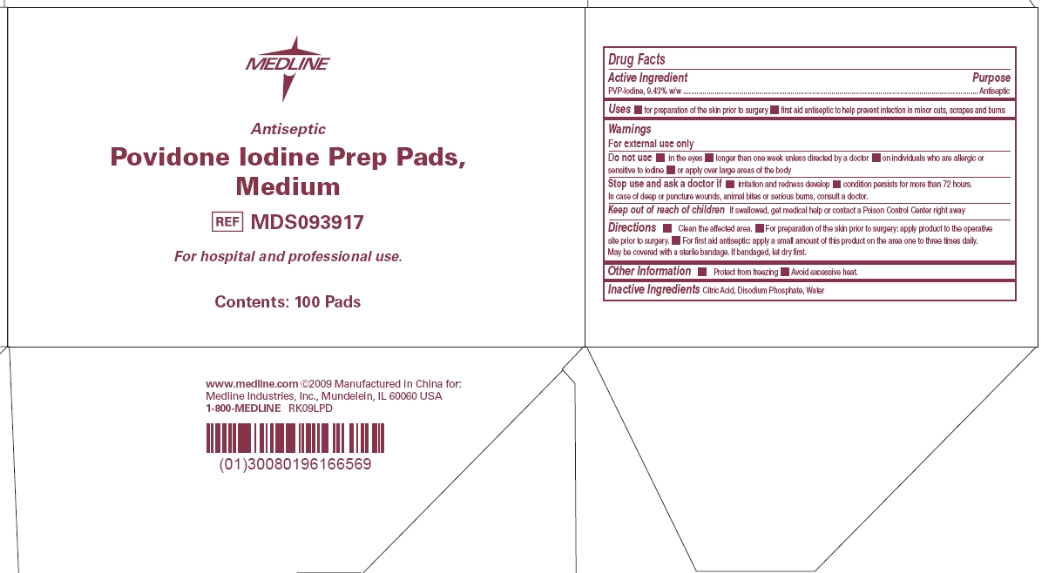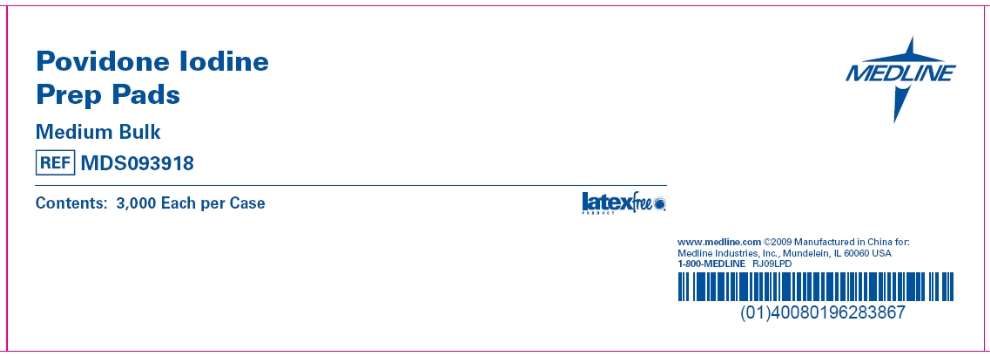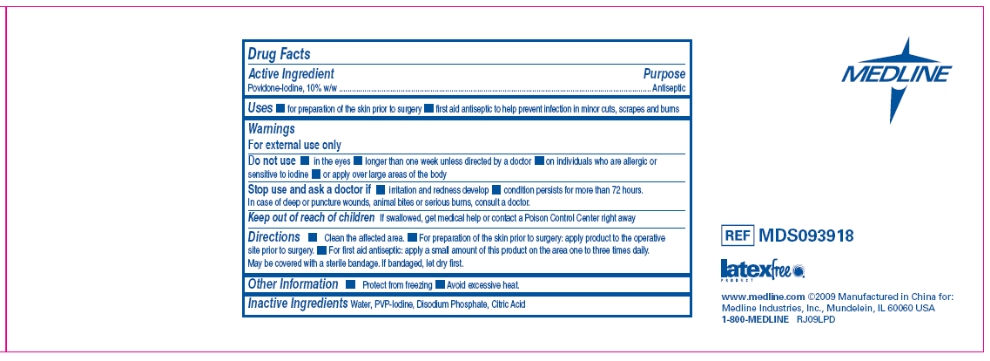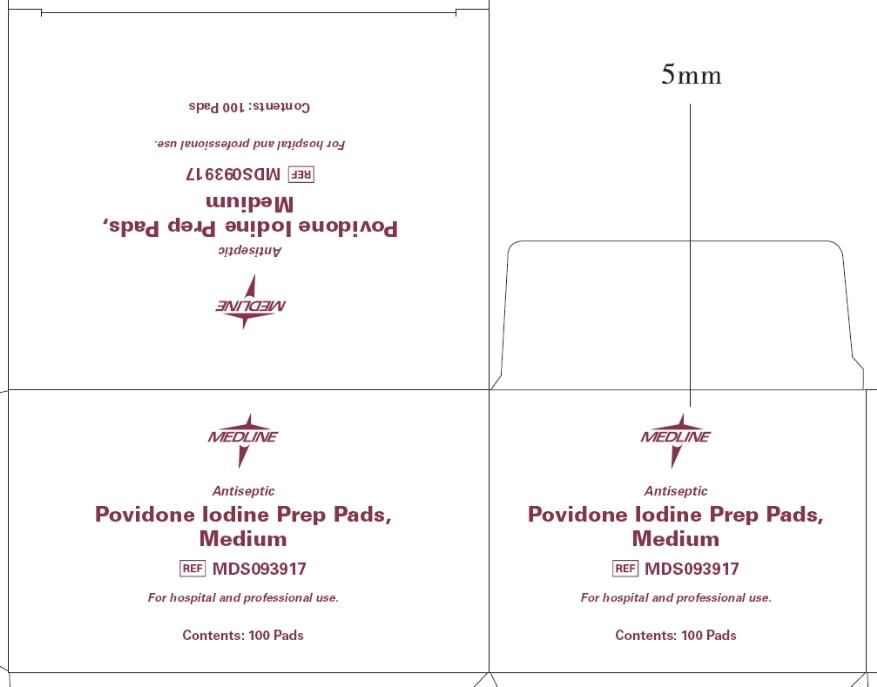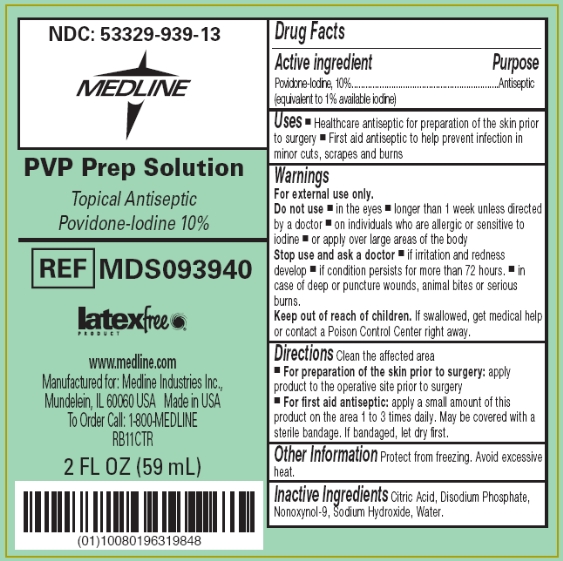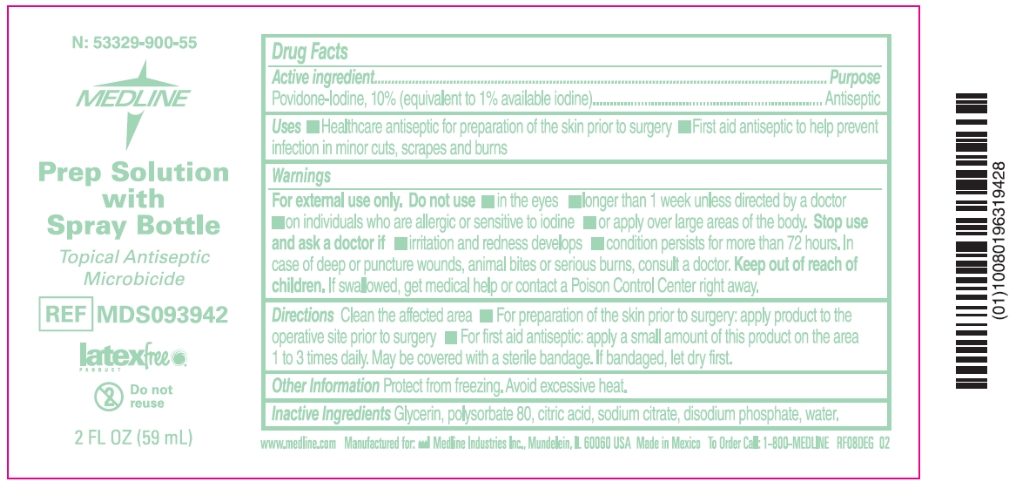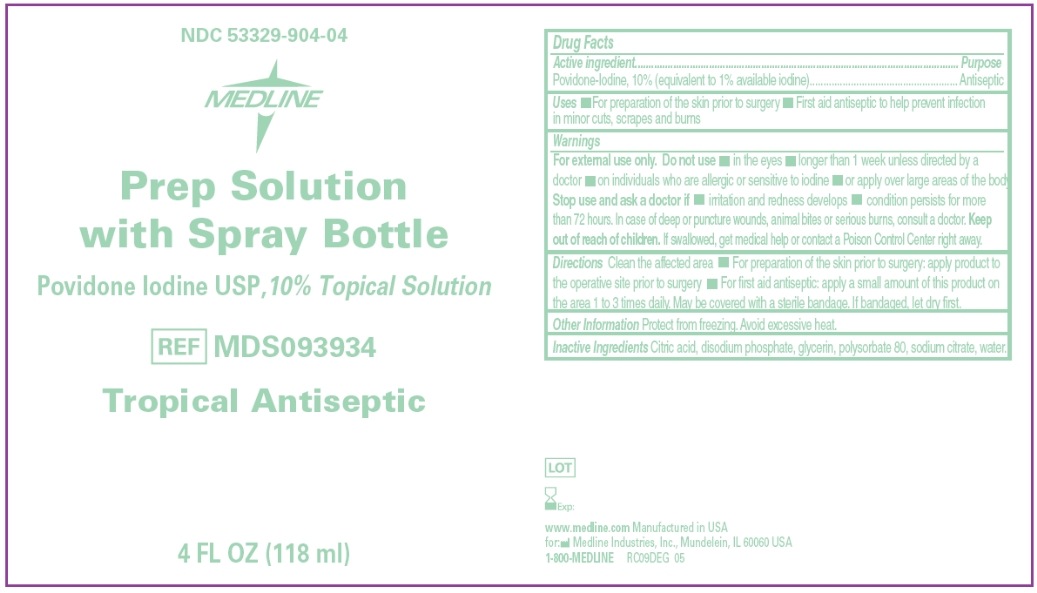 DRUG LABEL: Povidone-Iodine
NDC: 53329-945 | Form: SWAB
Manufacturer: Medline Industries, Inc.
Category: otc | Type: HUMAN OTC DRUG LABEL
Date: 20110823

ACTIVE INGREDIENTS: Povidone-Iodine 0.10 mL/1 1
INACTIVE INGREDIENTS: Citric Acid; Glycerin; Water; Sodium Hydroxide

Drug Facts

Active ingredient

Povidone Iodine 10% (equivalent to 1% available iodine)

Purpose

First Aid Antiseptic

Uses

- Healthcare antiseptic for preparation of the skin prior to surgery
- First aid antiseptic to help prevent infection in minor cuts, scrapes and burns

Warnings

For external use only.

Do not use

- in the eyes
- longer than 1 week unless directed by a doctor
- on individuals who are allergic or sensitive to iodine
- or apply over large areas of the body

Stop use and ask a doctor

- if irritation and redness develop
- if condition persists for more than 72 hours
- in case of deep or puncture wounds, animal bites or serious burns

Keep out of reach of children.

If swallowed, get medical help or contact a Poison Control Center right away.

Directions

Clean the affected area.

- For preparation of the skin prior to surgery: apply product to the operative site prior to surgery
- For first aid antiseptic: apply a small amount of this product on the area 1 to 3 times daily. May be covered with a sterile bandage. If bandaged, let dry first.

Other information

Protect from freezing. Avoid excessive heat.

Inactive ingredients

Citric Acid, Disodium Phosphate, Nonoxynol-9, Sodium Hydroxide, Water.

Questions

1-800-MEDLINE

Principal Display Panel - Swabstick Singles pouch

NDC53329-945-09

Medline

Antiseptic

Povidone-Iodine, USP

Swabsticks, Singles

MDS093901

latex free

For professional and hospital use.

Contents: 1 Swabstick

Principal Display Panel - Swabstick Singles box

NDC: 53329-945-29

Medline

Antiseptic

Povidone-Iodine, USP

Swabsticks, Singles

MDS093901

Discard appropriately after single use.

Protect from Freezing. Avoid excessive heat. For external use only.

latex free

Contents: 50 Each

Principal Display Panel - Swabstick Triples box

NDC 53329-946-75

Medline

Antiseptic

Povidone-Iodine, USP

Swabsticks, Triples

MDS093902

Discard appropriately after single use.

Protect from freezing. Avoid excessive heat. For external use only.

latex free

Contents: 25 Pouches

Principal Display Panel - Prep Pads, Medium box

Medline

Antiseptic

Povidone Iodine Prep Pads, Medium

MDS093917

For hospital and professional use.

Contents: 100 Pads

Principal Display Panel - Prep Pad Bulk case

Povidone Iodine

Prep PADS
Medium Bulk

MDS093918

Contents: 3,000 Each Per Case

Principal Display Panel - Prep Solution bottle

NDC: 53329-939-13

MEDLINE

PVP Prep Solution

Topical Antiseptic
Povidone-Iodine 10%

MDS093940

latexfree

www.medline.com

Manufactured for: Medline Industries, Inc.

Mundelein, IL 60060 USA Made in USA

To Order Call: 1-800-MEDLINE

RB11CTR

2 FL OZ (59 mL)

Principal Display Panel - Prep Solution label

N: 53329-900-55

Medline

Prep Solution

with

Spray Bottle

Topical Antiseptic

Microbicide

MDS093942

latex free

Do not reuse

2 FL OZ (59 mL)

Principal Display Panel - Prep Solution label

NDC 53329-904-04

Medline

Prep Solution

with Spray Bottle

Povidone Iodine USP, 10% Topical Solution

MDS093934

Topical Antiseptic

4 FL Oz (118 ml)